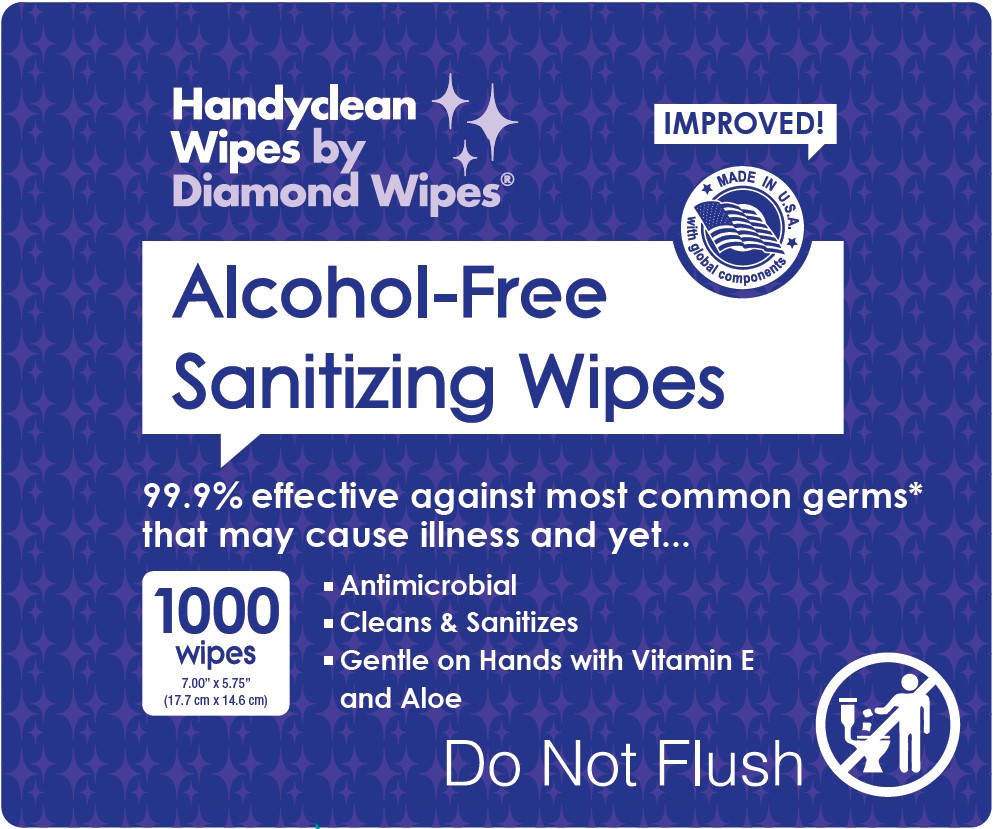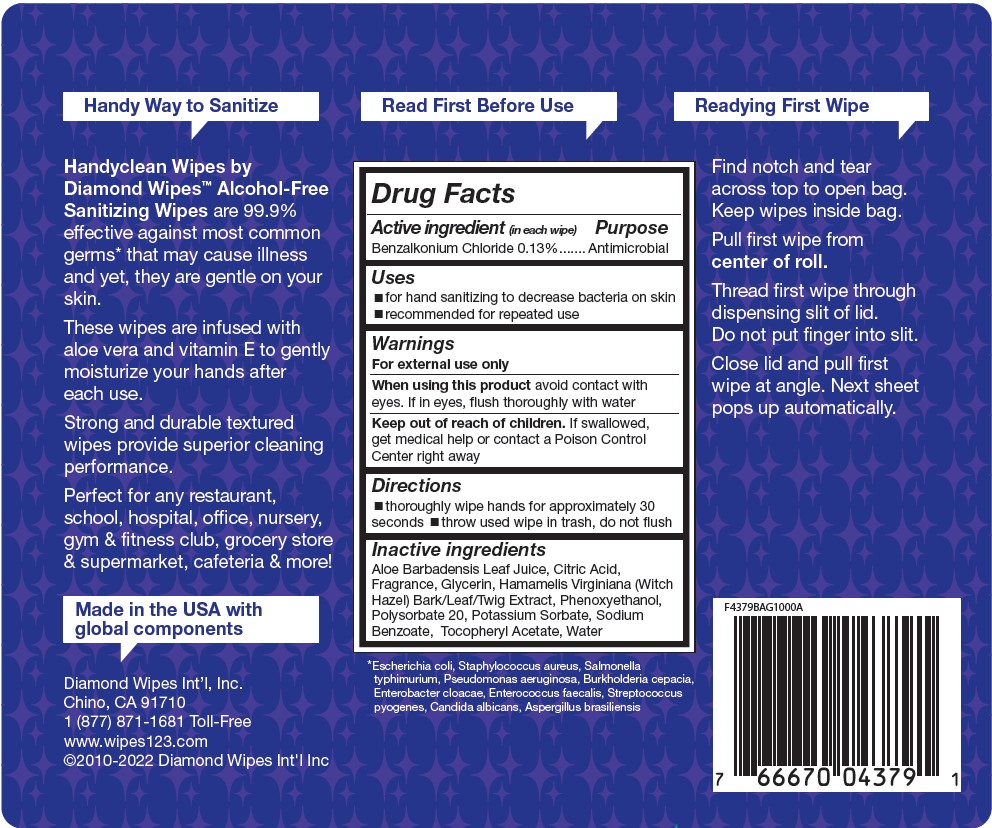 DRUG LABEL: ANTISEPTIC WIPE
NDC: 64709-108 | Form: CLOTH
Manufacturer: Diamond Wipes International
Category: otc | Type: HUMAN OTC DRUG LABEL
Date: 20250919

ACTIVE INGREDIENTS: BENZALKONIUM CHLORIDE 13 g/100 g
INACTIVE INGREDIENTS: ALOE VERA LEAF; CITRIC ACID MONOHYDRATE; GLYCERIN; HAMAMELIS VIRGINIANA TOP; PHENOXYETHANOL; POLYSORBATE 20; POTASSIUM SORBATE; SODIUM BENZOATE; WATER; .ALPHA.-TOCOPHEROL ACETATE

Alcohol-Free Sanitizing Wipes

Purpose

Antimicrobial

Uses

■for hand sanitizing to decrease bacteria on

■safe for repeated

Warnings

For external use only

When using this product avoid contact with eyes. If in eyes, flush thoroughly with water

Keep out of reach of children. If swallowed, get medical help or contact a Poison Control Center right away

Directions

■thoroughly wipe hands for approximately 30 seconds

■throw use wipe in trash, do not flush

Inactive ingredients

Aloe Barbadensis Leaf Juice, Citric Acid, Fragrance, Glycerin, Hamamelis, Virginiana (Witch Hazel) Bark/Leaf/Twig Extract, Phenoxyethanol, Polysorbate 20, Potassium Sorbate, Sodium Benzoate, Tocopheryl Acetate, Water

Label

Handyclean Wipes by Diamond Wipes®

Alcohol-Free Sanitizing Wipes

IMPROVED!

MADE IN U.S.A. with global components

99.9% effective against most common germs*

that may cause illness and yet...

1000 wipes 7.00" x 5.75" (17.7 cm x 14.6 cm)

■Antimicrobial ■Cleans & Sanitizes ■Gentle on Hands with Vitamin E and Aloe

Do Not Flush

Handy Way to Sanitize

Handyclean Wipes by Diamond Wipes™ Alcohol-Free Sanitizing Wipes are 99.9% effective against most common germs* that may cause illness and yet, they are gentle on your skin.
These wipes are infused with aloe vera and vitamin E to gently moisturize your hands after each use.
Strong and durable textured wipes provide superior cleaning performance.
Perfect for any restaurant, school, hospital, office, nursery, gym & fitness club, grocery store & supermarket, cafeteria & more!

MAKE IN U.S.A. with global components

Diamond Wipe Int'l, Inc.

Chino, CA 91710

1 (877) 871-1681 Toll-Free

www.wipes123.com

©2010-2022 Diamond Wipe Int'l, Inc

Read First Before Use

Drug Facts

Active Ingredient (in each wipe) Purpose

Benzalkonium Chloride 0.13%.......Antimicrobial

Uses

■for hand sanitizing to decrease bacteria on skin
■recommended for repeated use

Warnings

For external use only
When using this product avoid contact with eyes. If in eyes, flush thoroughly with water
Keep out of reach of children. If swallowed, get medical help or contact a Poison Control Center right away

Directions

■thoroughly wipe hands for approximately 30 seconds ■throw used wipe in trash, do not flush

Inactive ingredients

Aloe Barbadensis Leaf Juice, Citric Acid, Fragrance, Glycerin, Hamamelis Virginiana (Witch Hazel) Bark/Leaf/Twig Extract, Phenoxyethanol, Polysorbate 20, Potassium Sorbate, Sodium Benzoate, Tocopheryl Acetate, Water

*Escherichia coli, Staphylococcus aureus, Salmonella typhimurium, Pseudomonas aeruginosa, Burkholderia cepacia, Enterobacter cloacae, Enterococcus faecalis, Streptococcus pyogenes, Candida albicans, Aspergillus brasiliensis

Readying First Wipe

Find notch and tear across top to open bag. Keep wipes inside bag. Pull first wipe from center of roll. Thread first wipe through dispensing slit of lid. Do not put finger into slit. Close lid and pull first wipe at angle. Next sheet pops up automatically.

F4379BAG1000A

7 6667004379 1